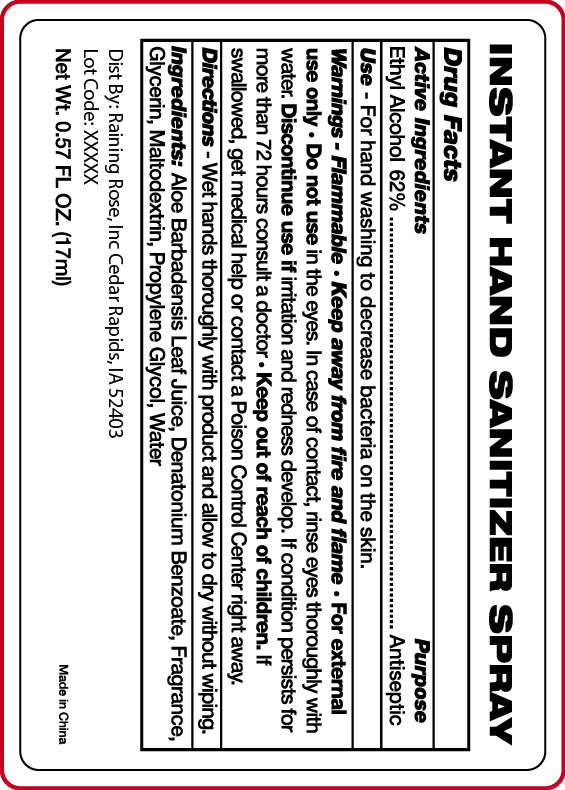 DRUG LABEL: Hand Sanitizer
NDC: 65692-2053 | Form: LIQUID
Manufacturer: Raining Rose, Inc
Category: otc | Type: HUMAN OTC DRUG LABEL
Date: 20231107

ACTIVE INGREDIENTS: ALCOHOL 62 mL/100 mL
INACTIVE INGREDIENTS: DENATONIUM BENZOATE; MALTODEXTRIN; WATER; PROPYLENE GLYCOL; ALOE VERA LEAF; GLYCERIN

Hand Sanitizer Vanilla

ACTIVE INGREDIENT

Ethyl Alcohol 62%

PURPOSE

Antiseptic

INDICATIONS AND USAGE

For hand washing to decrease bacteria on the skin.

Warnings• For external use only
• Flammable, keep away from fire or flame
• Do not use in eyes. In case of contact, rinse eyes thorougly with water.

• Discontinue use if irritation and redness develop.If condition persists for more than 72 hours consult a doctor.

• Keep out of reach of children. If swallowed, get medical help or contact a Poison Control Center right away.

Keep Out of Reach of Children. If swallowed, get medical help or contact a Poison Control Center right away.

DOSAGE AND ADMINISTRATION

Wet hands thoroughly with product and allow to dry without wiping.

INACTIVE INGREDIENT

Inactive Ingredients: Aloe Barbadensis Leaf Juice, Denatonium Benzoate, Fragrance, Glycerin, Maltodextrin, Propylene Glycol, Water